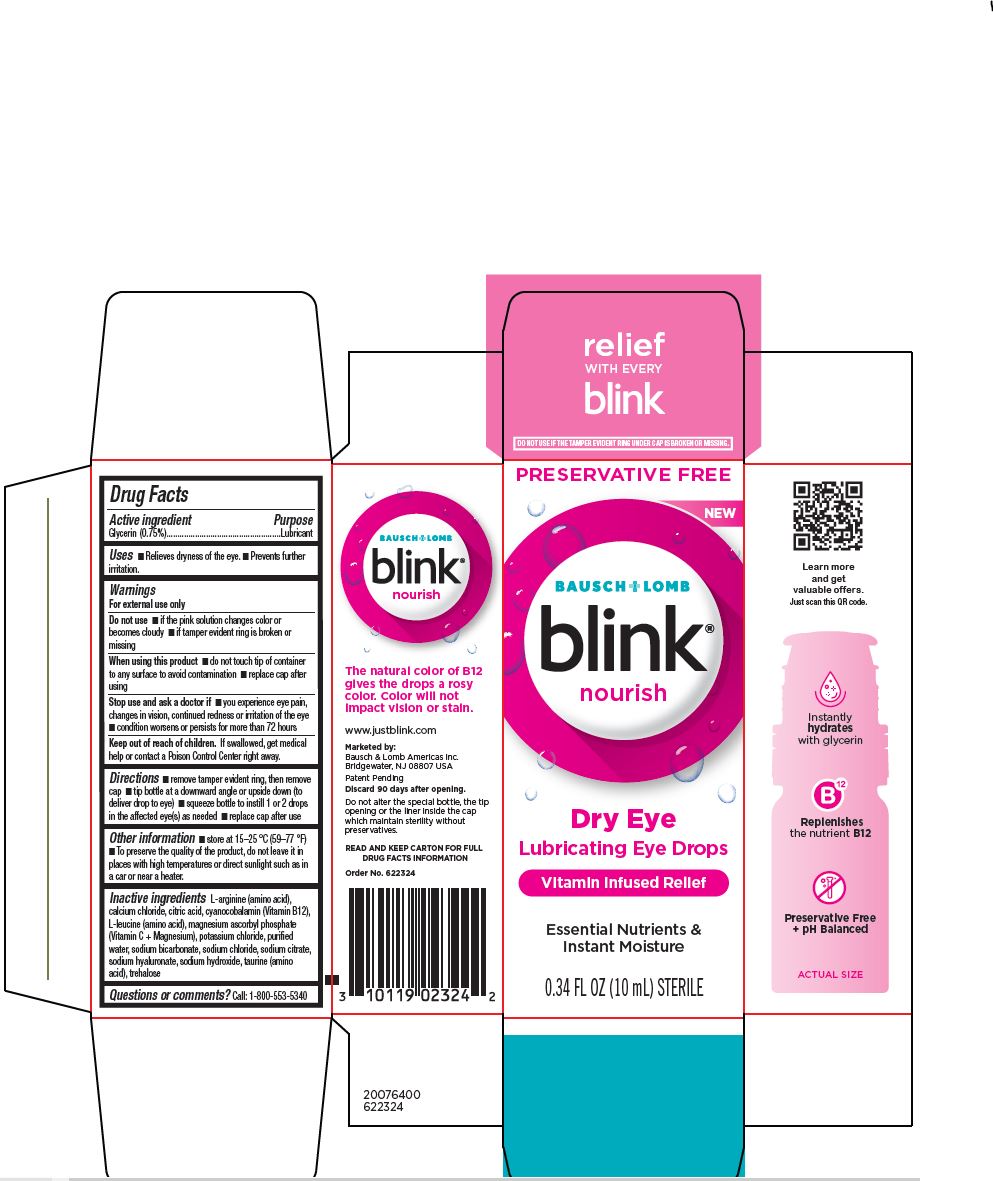 DRUG LABEL: Blink Nourish Dry Eye
NDC: 29943-008 | Form: SOLUTION/ DROPS
Manufacturer: Bausch & Lomb Incorporated
Category: otc | Type: HUMAN OTC DRUG LABEL
Date: 20250225

ACTIVE INGREDIENTS: GLYCERIN 7.5 mg/1 mL
INACTIVE INGREDIENTS: ARGININE; CALCIUM CHLORIDE; CITRIC ACID MONOHYDRATE; CYANOCOBALAMIN; LEUCINE; MAGNESIUM ASCORBYL PHOSPHATE; POTASSIUM CHLORIDE; WATER; SODIUM BICARBONATE; SODIUM CHLORIDE; HYALURONATE SODIUM; SODIUM CITRATE, UNSPECIFIED FORM; SODIUM HYDROXIDE; TAURINE; TREHALOSE

blink®
nourish

Active ingredient

Glycerin (0.75%)

Purpose

Lubricant

Uses

■ Relieves dryness of the eye.
■ Prevents further irritation.

Warnings

For external use only
Do not use
■ if the pink solution changes color or becomes cloudy
■ if tamper evident ring is broken or missing
When using this product
■ do not touch tip of container to any surface to avoid contamination
■ replace cap after using

Stop use and ask a doctor if
■ you experience eye pain, changes in vision, continued redness or irritation of the eye
■ condition worsens or persists for more than 72 hours

Keep out of reach of children

If swallowed, get medical help or contact a Poison Control Center right away.

Directions

■ remove tamper evident ring, then remove cap
■ tip bottle at a downward angle or upside down (to deliver drop to eye)
■ squeeze bottle to instill 1 or 2 drops in the affected eye(s) as needed
■ replace cap after use

Other information

■ store at 15–25 °C (59–77 °F)
■ To preserve the quality of the product, do not leave it in places with high temperatures or direct sunlight such as in a car or near a heater.

Inactive Ingredients

L-arginine (amino acid), calcium chloride, citric acid, cyanocobalamin (Vitamin B12), L-leucine (amino acid), magnesium ascorbyl phosphate (Vitamin C + Magnesium), potassium chloride, purified water, sodium bicarbonate, sodium chloride, sodium citrate, sodium hyaluronate, sodium hydroxide, taurine (amino acid), trehalose

Questions or comments?

Call: 1-800-553-5340